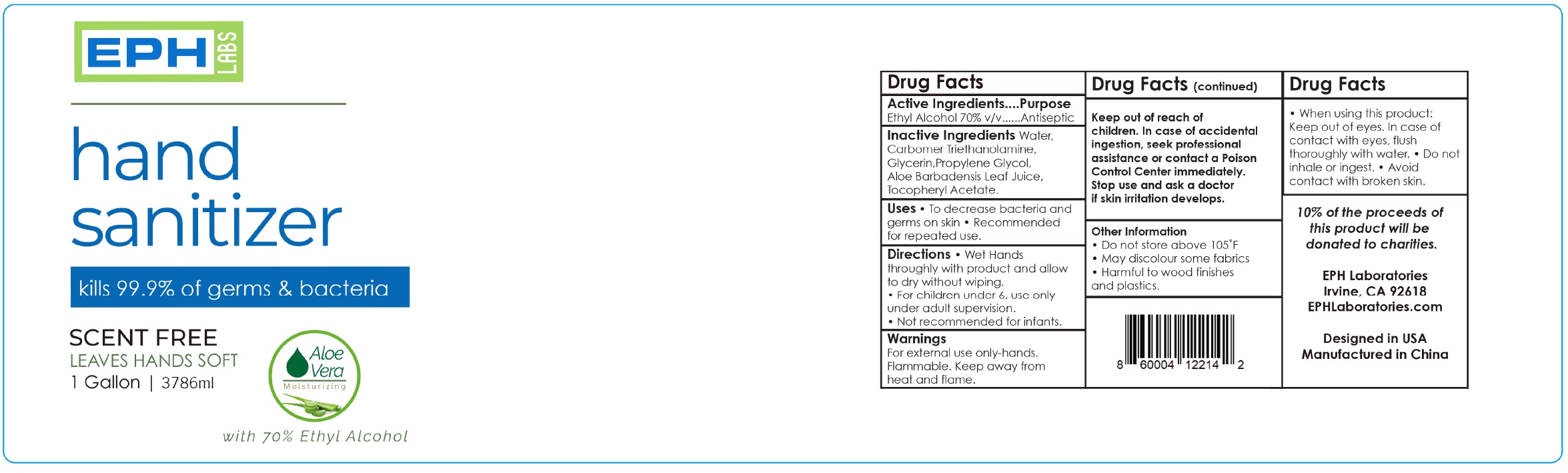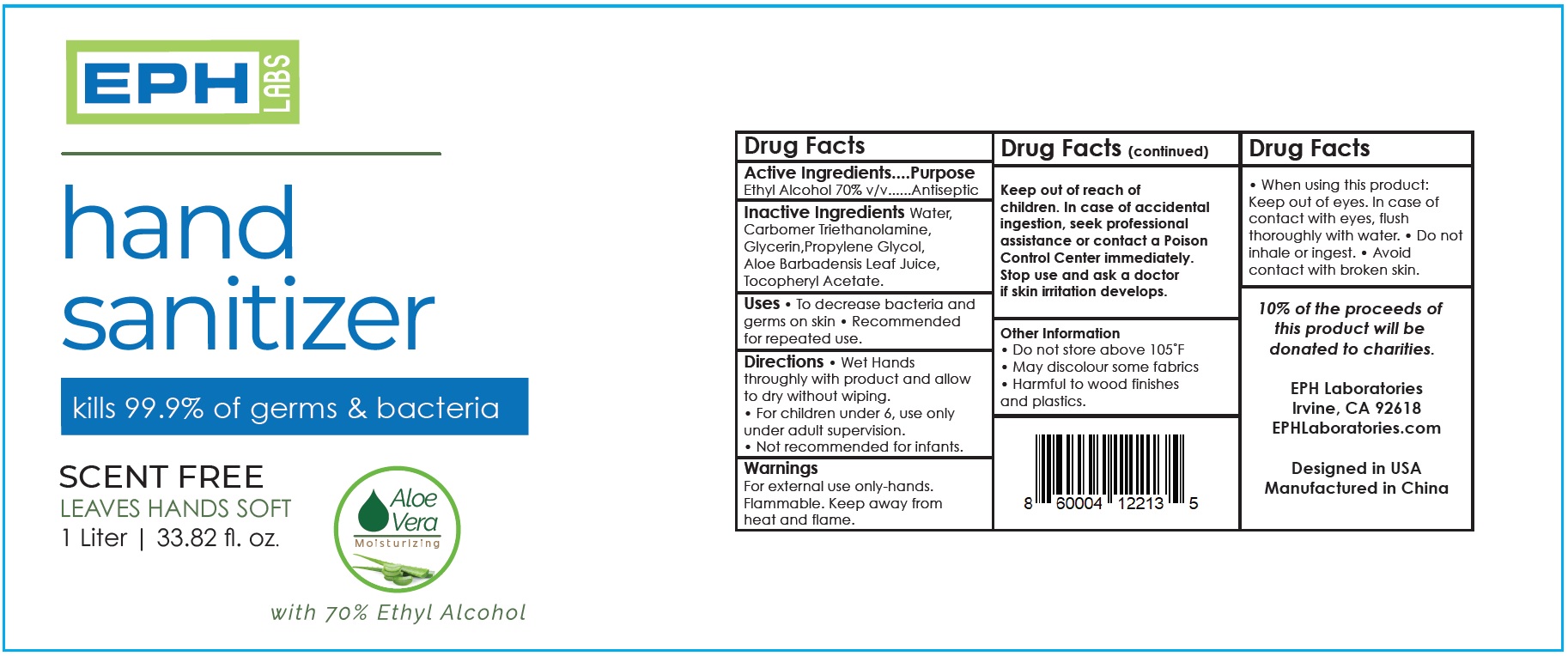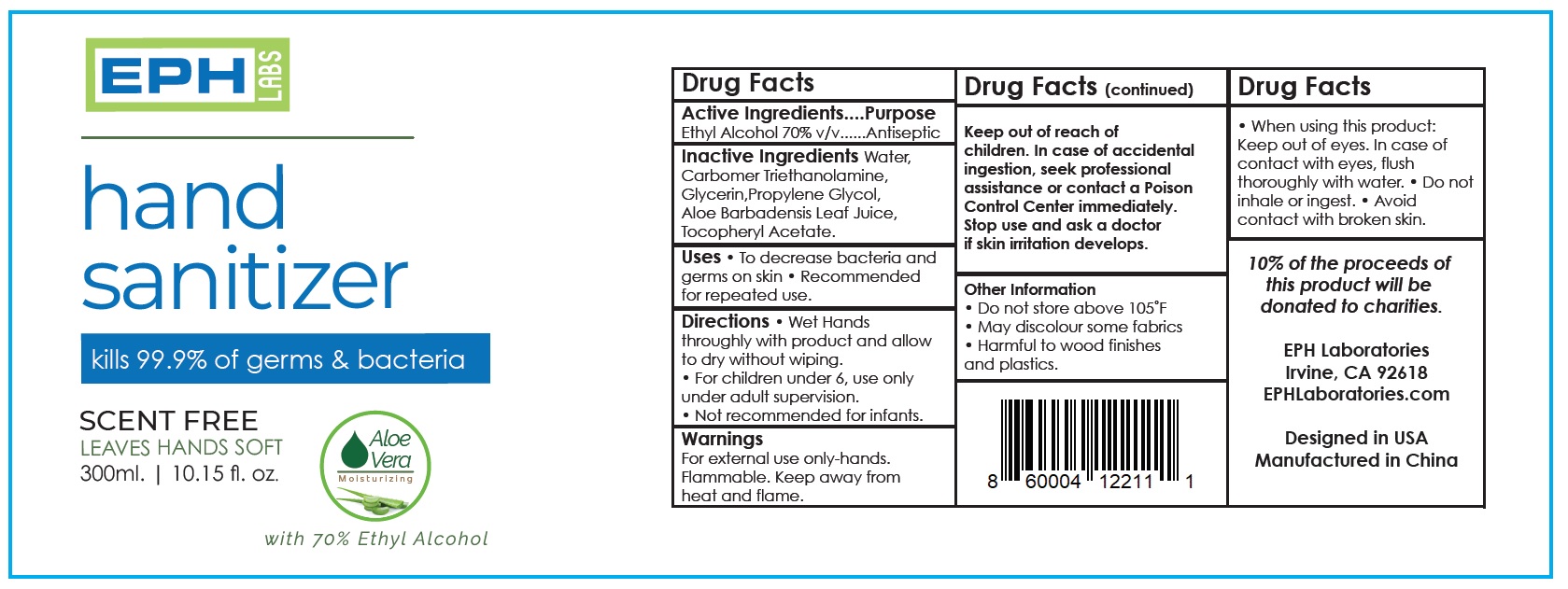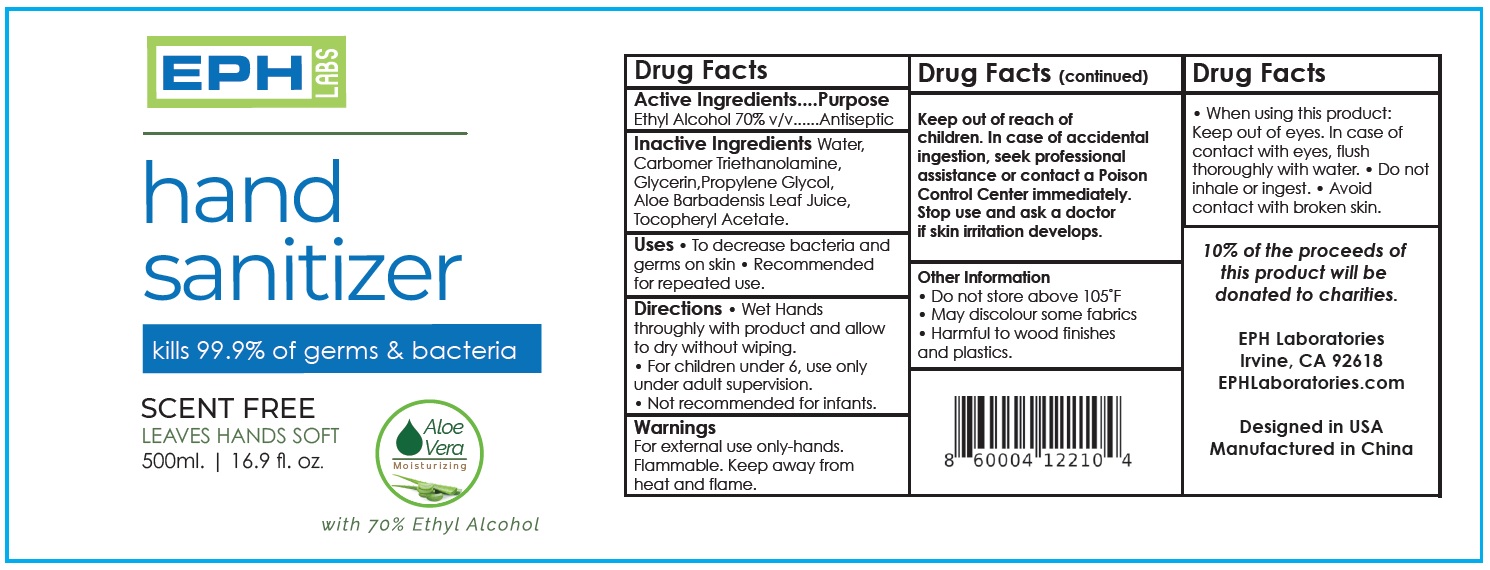 DRUG LABEL: EPH Labs Hand Sanitizer
NDC: 79759-002 | Form: GEL
Manufacturer: EPH Laboratories
Category: otc | Type: HUMAN OTC DRUG LABEL
Date: 20200727

ACTIVE INGREDIENTS: ALCOHOL 0.7 mL/1 mL
INACTIVE INGREDIENTS: WATER; CARBOMER HOMOPOLYMER, UNSPECIFIED TYPE; TROLAMINE; GLYCERIN; PROPYLENE GLYCOL; ALOE VERA LEAF; .ALPHA.-TOCOPHEROL ACETATE

EPH Labs Hand Sanitizer

Active Ingredients

Ethyl Alcohol 70% v/v

Purpose

Antiseptic

Inactive Ingredients

Water, Carbomer Triethanolamine, Glycerin,Propylene Glycol, Aloe Barbadensis Leaf Juice, Tocopheryl Acetate.

Uses

• To decrease bacteria and germs on skin • Recommended for repeated use.

Directions

• Wet Hands throughly with product and allow to dry without wiping. • For children under 6, use only under adult supervision. • Not recommended for infants.

Warnings

For external use only-hands. Flammable. Keep away from heat and flame.

Keep out of reach of children.

In case of accidental ingestion, seek professional assistance or contact a Poison Control Center immediately.

Stop use and ask a doctor

if skin irritation develops.

When using this product:

Keep out of eyes. In case of contact with eyes, flush thoroughly with water. • Do not inhale or ingest. • Avoid contact with broken skin.

Other Information

• Do not store above 105˚F
• May discolour some fabrics
• Harmful to wood finishes and plastics.